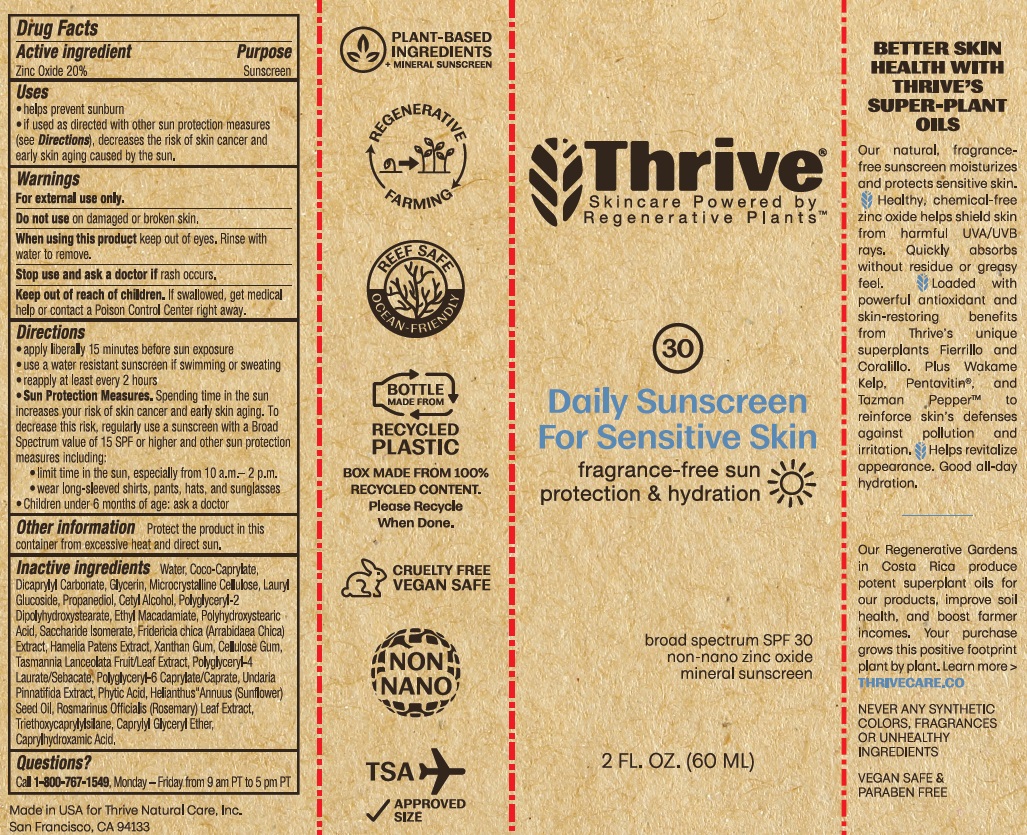 DRUG LABEL: Thrive Daily Sunscreen For Sensitive Skin SPF 30
NDC: 84138-0002 | Form: CREAM
Manufacturer: Thrive Natural Care, Inc
Category: otc | Type: HUMAN OTC DRUG LABEL
Date: 20251023

ACTIVE INGREDIENTS: ZINC OXIDE 20 g/100 mL
INACTIVE INGREDIENTS: SACCHARIDE ISOMERATE; LAURYL GLUCOSIDE; CAPRYLHYDROXAMIC ACID; XANTHAN GUM; CARBOXYMETHYLCELLULOSE SODIUM, UNSPECIFIED; HAMELIA PATENS LEAF; POLYHYDROXYSTEARIC ACID (2300 MW); DICAPRYLYL CARBONATE; MICROCRYSTALLINE CELLULOSE; PROPANEDIOL; ETHYL MACADAMIATE; TASMANNIA LANCEOLATA FRUIT; TRIETHOXYCAPRYLYLSILANE; GLYCERIN; FYTIC ACID; POLYGLYCERYL-2 DIPOLYHYDROXYSTEARATE; POLYGLYCERYL-4 LAURATE; ROSEMARY; CAPRYLYL GLYCERYL ETHER; SUNFLOWER OIL; POLYGLYCERYL-6 CAPRYLATE; FRIDERICIA CHICA LEAF; CETYL ALCOHOL; WATER; COCO-CAPRYLATE; UNDARIA PINNATIFIDA

Thrive Daily Sunscreen For Sensitive Skin SPF 30

Active Ingredient

Zinc Oxide 20%

Purpose

Sunscreen

Uses

helps prevent sunburn

if used as directed with other sun protection measures (see Directions), decreases the risk of skin cancer and early skin aging caused by the sun.

Warnings

For external use only.

Do not use

on damaged or broken skin.

When using this product

keep out of eyes. Rinse with water to remove.

Stop use and ask a doctor if

rash occurs.

Keep out of reach of children.

If swallowed, get medical help or contact a Poison Control Center right away.

Directions

apply liberally 15 minutes before sun exposure

use a water resistant sunscreen if swimming or sweating

reapply at least every 2 hours

Sun Protection Measures. Spending time in the sun increases your risk of skin cancer and early skin aging. To decrease this risk, regularly use a sunscreen with a Broad Spectrum value of 15 SPF or higher and other sun protection measures including:

- limit time in the sun, especially from 10 a.m.- 2 p.m.
- wear long-sleeved shirts, pants, hats and sunglasses

Children under 6 months of age: ask a doctor

Other information

Protect the product in this container from excessive heat and direct sun.

Inactive ingredients

Water, Coco-Caprylate, Dicaprylyl Carbonate, Glycerin, Microcrystalline Cellulose, Lauryl Glucoside, Propanediol, Cetyl Alcohol, Polyglyceryl-2 Dipolyhydroxystearate, Ethyl Macadamiate, Polyhydroxystearic Acid, Saccharide Isomerate, Fridericia Chica (Arrabidaea Chica) Extract, Hamelia Patens Extract, Xanthan Gum, Cellulose Gum, Tasmannia Lanceolata Fruit/Leaf Extract, Polyglyceryl-4 Laurate/Sebacate, Polyglyceryl-6 Caprylate/Caprate, Undaria Pinnatifida (Wakame) Extract, Phytic Acid, Helianthus Annuus (Sunflower) Seed Oil, Rosmarinus Officinalis (Rosemary) Leaf Extract, Triethoxycaprylylsilane, Caprylyl Glyceryl Ether, Caprylhydroxamic Acid.

Questions?

Call 1-800-767-1549, Monday - Friday from 9 am PT to 5 pm PT

Principal Display Panel

Thrive

Skincare Powered by

Regenerative PlantsTM

30

Daily Sunscreen

For Sensitive Skin

fragrance-free sun

protection & hydration

broadspectrum SPF 30

non-nano zinc oxide

mineral sunscreen

2 FL. OZ. (60 ML)